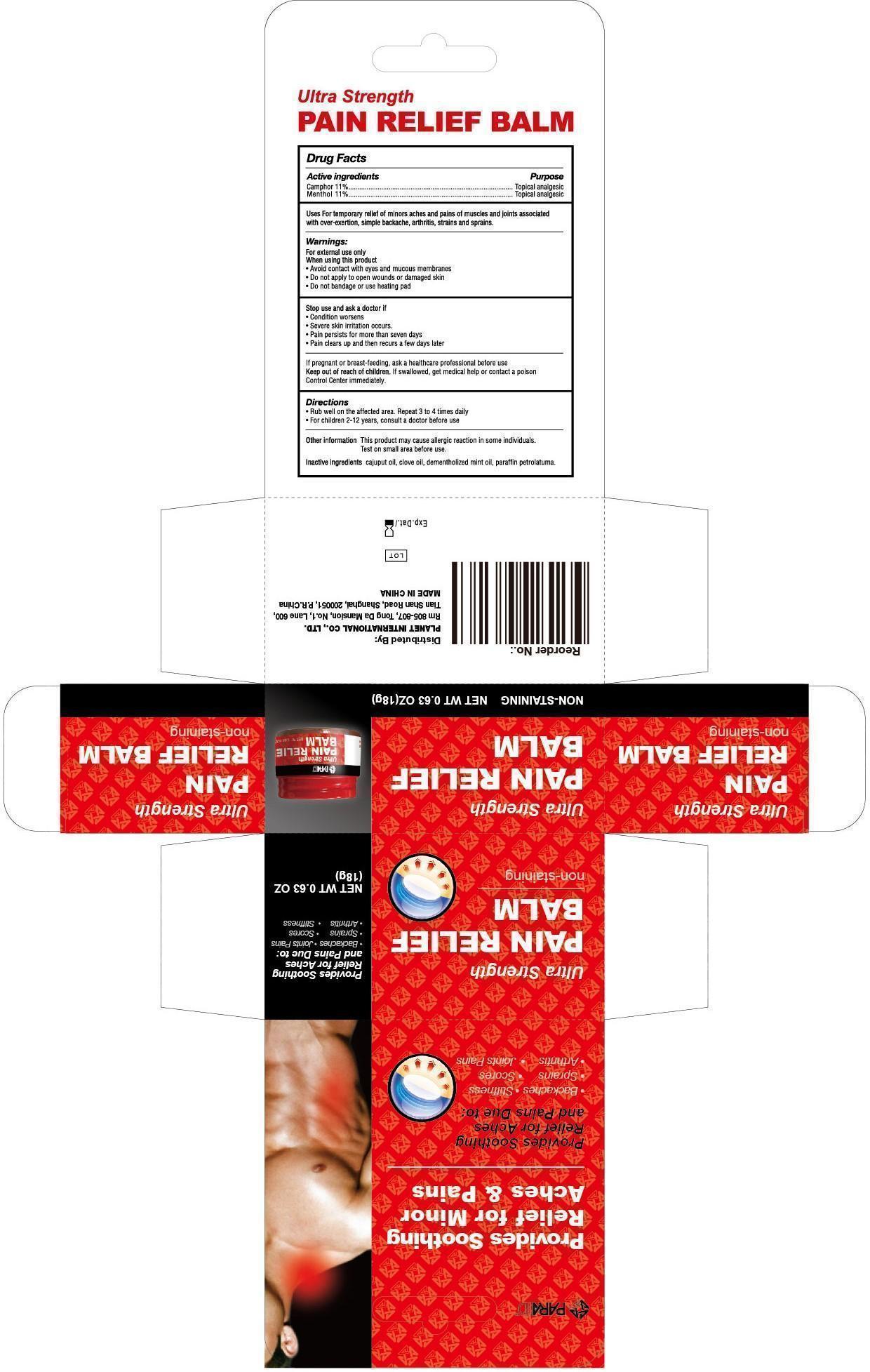 DRUG LABEL: Ultra Strength Pain Relief Balm
NDC: 52486-013 | Form: GEL
Manufacturer: McCure Health Solutions Inc.
Category: otc | Type: HUMAN OTC DRUG LABEL
Date: 20161228

ACTIVE INGREDIENTS: CAMPHOR (NATURAL) 110 mg/1 g; MENTHOL 110 mg/1 g
INACTIVE INGREDIENTS: CAJUPUT OIL; CLOVE OIL

Ultra Strength Pain Relief Balm

Active ingredients

Camphor 11%

Menthol 11%

Purpose

Topical analgesic

Uses

For temporary relief minors aches and pains of muscles and joints associated with over-exertion, simple backache, arthritis, strains and sprains.

Warnings

For external use only

When using this product

- Avoid contact with eyes and mocous membranes
- Do not apply to open wounds or damaged skin
- Do not bandage or use heating pad

Stop use and ask a doctor if

- Condition worsens
- Severe skin irritation occurs.
- Pain persists for more than seven days
- Pain clears up and then recurs a few days later

If pregnant or breast-feeding,

ask a healthcare professional before use

Keep out of reach of children.

If swallowed, get medical help or contact a poison Control Center immediately.

Directions

- Rub well on the affected area. Repeat 3 to 4 times daily

Other information

This product may cause allergic reaction in some individuals. Test on small area before use.

Inactive ingredients

CAJUPUT OIL, CLOVE OIL, DEMENTHOLIZED MINT OIL, PARAFFIN PETROLATUMA